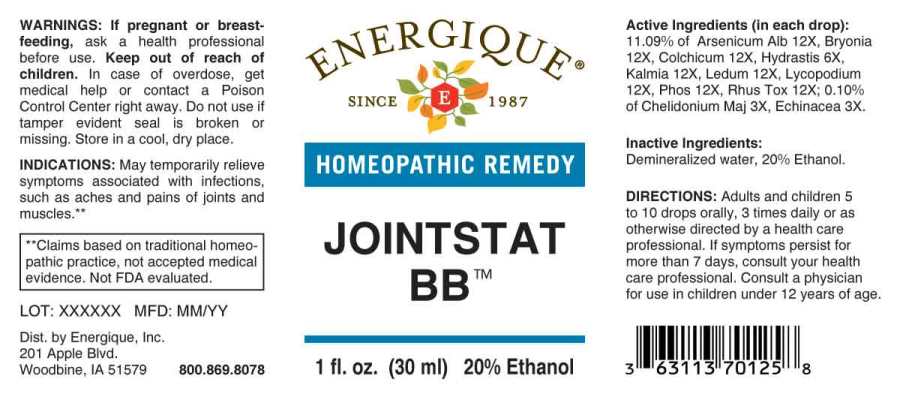 DRUG LABEL: Jointstat BB
NDC: 44911-0589 | Form: LIQUID
Manufacturer: Energique, Inc.
Category: homeopathic | Type: HUMAN OTC DRUG LABEL
Date: 20241028

ACTIVE INGREDIENTS: CHELIDONIUM MAJUS WHOLE 3 [hp_X]/1 mL; ECHINACEA ANGUSTIFOLIA WHOLE 3 [hp_X]/1 mL; GOLDENSEAL 6 [hp_X]/1 mL; ARSENIC TRIOXIDE 12 [hp_X]/1 mL; BRYONIA ALBA ROOT 12 [hp_X]/1 mL; COLCHICUM AUTUMNALE BULB 12 [hp_X]/1 mL; KALMIA LATIFOLIA LEAF 12 [hp_X]/1 mL; LEDUM PALUSTRE TWIG 12 [hp_X]/1 mL; LYCOPODIUM CLAVATUM SPORE 12 [hp_X]/1 mL; PHOSPHORUS 12 [hp_X]/1 mL; TOXICODENDRON PUBESCENS LEAF 12 [hp_X]/1 mL
INACTIVE INGREDIENTS: WATER; ALCOHOL

Drug Facts:

ACTIVE INGREDIENTS:

(in each drop): 11.09% Arsenicum Album 12X, Bryonia (Alba) 12X, Colchicum Autumnale 12X, Hydrastis Canadensis 6X, Kalmia Latifolia 12X, Ledum Palustre 12X, Lycopodium Clavatum 12X, Phosphorus 12X, Rhus Tox 12X; 0.10% of Chelidonium Majus 3X, Echinacea (Angustifolia) 3X.

INDICATIONS:

May temporarily relieve symptoms associated with infections such as aches and pains of joints and muscles.**

**Claims based on traditional homeopathic practice, not accepted medical evidence. Not FDA evaluated.

WARNINGS:

If pregnant or breastfeeding, ask a health professional before use.

Keep out of reach of children. In case of overdose, get medical help or contact a Poison Control Center right away.

Do not use if tamper evident seal is broken or missing.

Store in a cool, dry place.

Keep out of reach of children. In case of overdose, get medical help or contact a Poison Control Center right away.

DIRECTIONS:

Adults and children 5 to 10 drops orally, 3 times daily or as otherwise directed by a health care professional. If symptoms persist, consult your health care professional. Consult a physician for use in children under 12 years of age.

INDICATIONS:

May temporarily relieve symptoms associated with infections such as aches and pains of joints and muscles.**

**Claims based on traditional homeopathic practice, not accepted medical evidence. Not FDA evaluated.

INACTIVE INGREDIENTS:

Demineralized water, 20% Ethanol

QUESTIONS:

Dist. by Energique, Inc.
201 Apple Blvd.
Woodbine, IA 51579 800.869.8078

PACKAGE LABEL DISPLAY:

ENERGIQUE

SINCE 1987

HOMEOPATHIC REMEDY

JOINTSTAT BB

1 fl. oz. (30 ml)